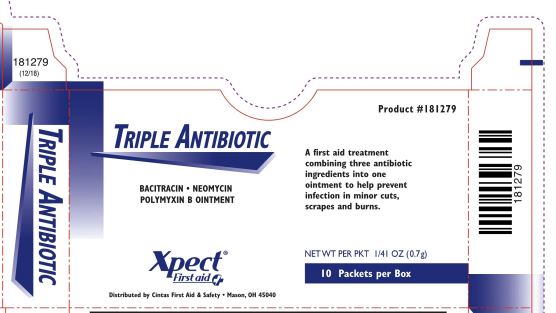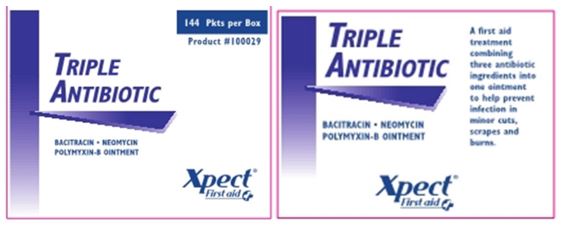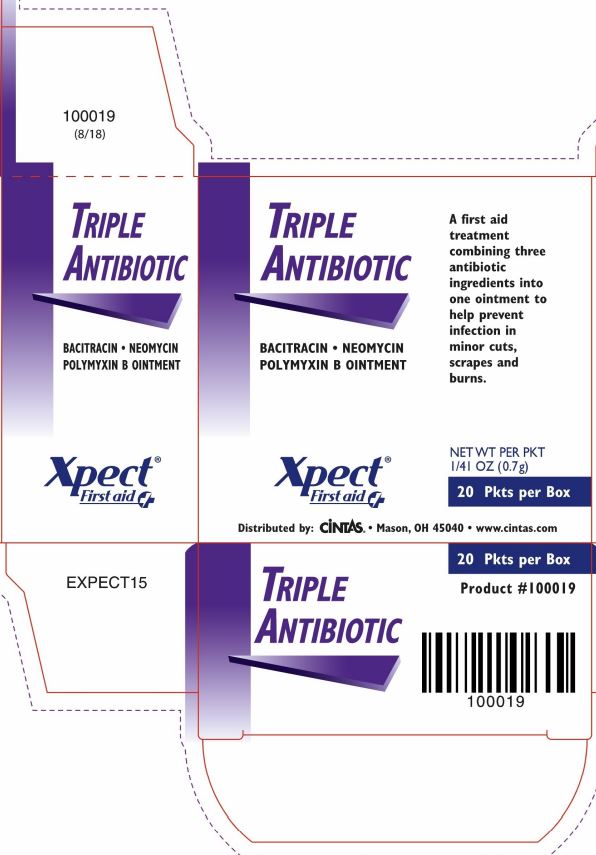 DRUG LABEL: Xpect Triple Antibiotic
NDC: 42961-222 | Form: OINTMENT
Manufacturer: Cintas Corporation
Category: otc | Type: HUMAN OTC DRUG LABEL
Date: 20250926

ACTIVE INGREDIENTS: BACITRACIN ZINC 400 [iU]/1 g; NEOMYCIN SULFATE 5 mg/1 g; POLYMYXIN B SULFATE 5000 [iU]/1 g
INACTIVE INGREDIENTS: PETROLATUM

Xpect Triple Antibiotic

Active ingredients (each gram contains)

Bacitracin zinc 400 units

Neomycin sulfate 5 mg (equivalent to 3.5 mg of neomycin base)

Polymyxin-B sulfate 5,000 units

Purpose

first aid antibiotic

first aid antibiotic

first aid antibiotic

Uses

first aid to help prevent infection in minor cuts, scrapes, and burns

Warnings

For external use only

Do not use

- in the eyes or apply over large areas of the body
- if you are allergic to any of the ingredients
- longer than 1 week unless directed by a doctor

Ask a doctor before use if you have

- deep or puncture wounds
- animal bites
- serious burns

Stop use and ask a doctor if

- condition persists or gets worse
- rash or other allergic reaction develops

Keep out of reach of children.

If swallowed, get medical help or contact a Poison Control Center right away.

Directions

- clean the affected area
- may be covered with a sterile bandage
- apply a small amount (an amount equal to the surface area of the tip of a finger) 1-3 times daily

Other information

- do not use if packet is torn, cut or opened
- store at room temperature 15-30° C (59-86°F)
- see packet for Lot Number and expiration date

Inactive ingredients

petrolatum

Questions?

1-877-973-2811

Principal Display Panel - 10 Count Box

181279

(12/18)

TRIPLE ANTIBIOTIC

TRIPLE ANTIBIOTIC

BACITRACIN • NEOMYCIN

POLUMYXIN B OINTMENT

Product #181279

A first aid treatment combining three antibiotic ingredients into one ointment to help prevent infection in minor cuts, scrapes and burns.

Xpect® First aid

Distributed by Cintas First Aid & Safety • Mason, OH 45040

NET WT PER PKT 1/41 OZ (0.7g)

10 Packets per Box

181279

Package Principal Display Panel - 20 Count Box

100019

(8/18)

TRIPLE ANTIBIOTIC

BACITRACIN • NEOMYCIN

POLYMYXIN B OINTMENT

Xpect® First aid

EXPECT15

TRIPLE ANTIBIOTIC

BACITRACIN • NEOMYCIN

POLYMYXIN B OINTMENT

A first aid treatment combining three antibiotic ingredients into one ointment to help prevent infection in minor cuts, scrapes and burns.

Xpect® First aid

Distributed by Cintas Mason, OH 45040 www.cintas.com

NET WT PER PKT

1/41 OZ (0.7g)

20 Pkts per Box

TRIPLE ANTIBIOTIC

20 Pkts per Box

Product #100019

100019

Package Principal Display Panel 42961-222-04

144 Pkts per Box

Product #100029

TRIPLE ANTIBIOTIC

BACITRACIN • NEOMYCIN

POLYMYXIN-B OINTMENT

Xpect® First aid

TRIPLE ANTIBIOTIC

BACITRACIN • NEOMYCIN

POLYMYXIN-B OINTMENT

A first aid treatment combining three antibiotic ingredients into one ointment to help prevent infection in minor cuts, scrapes and burns.

Xpect® First aid